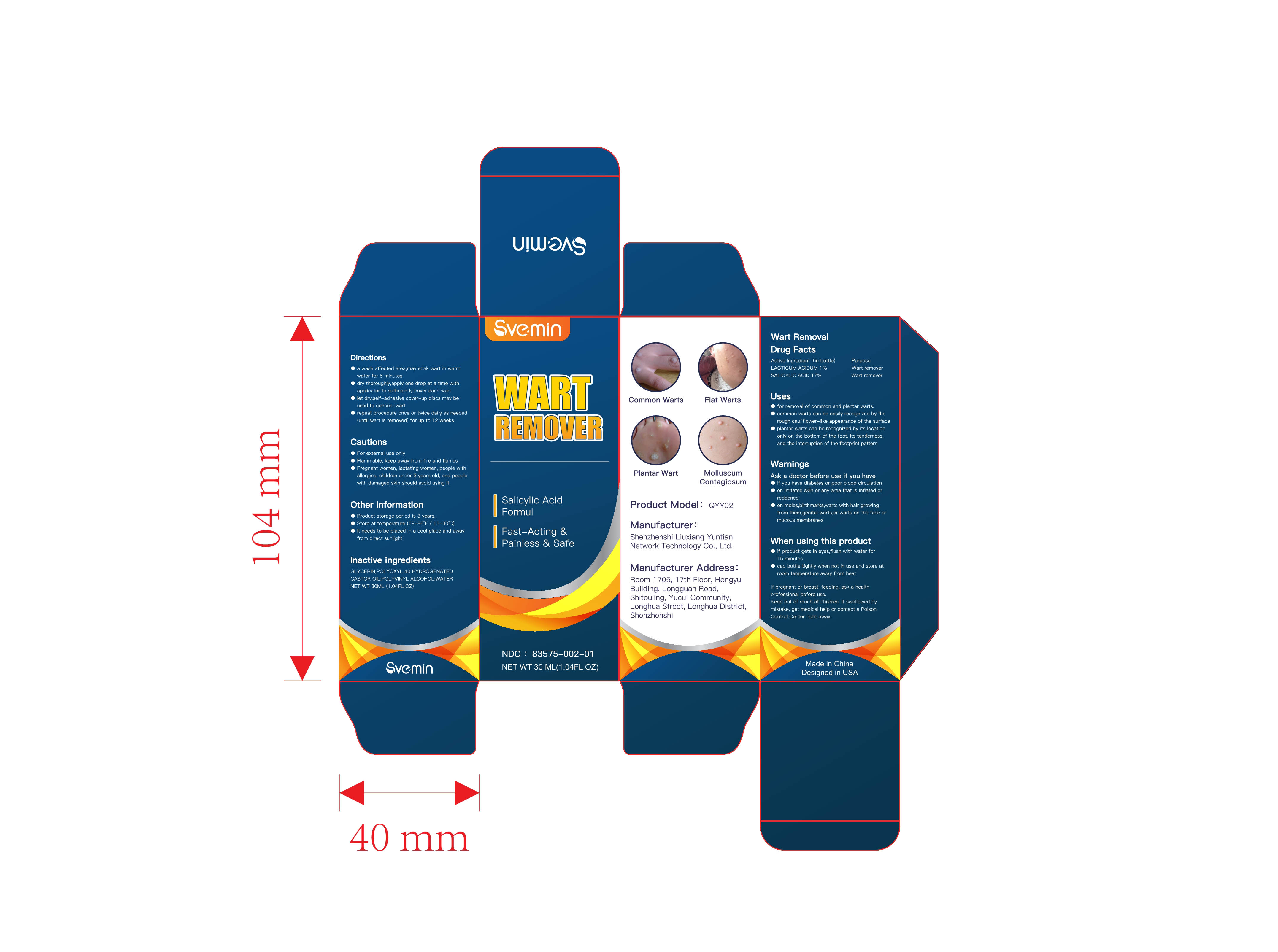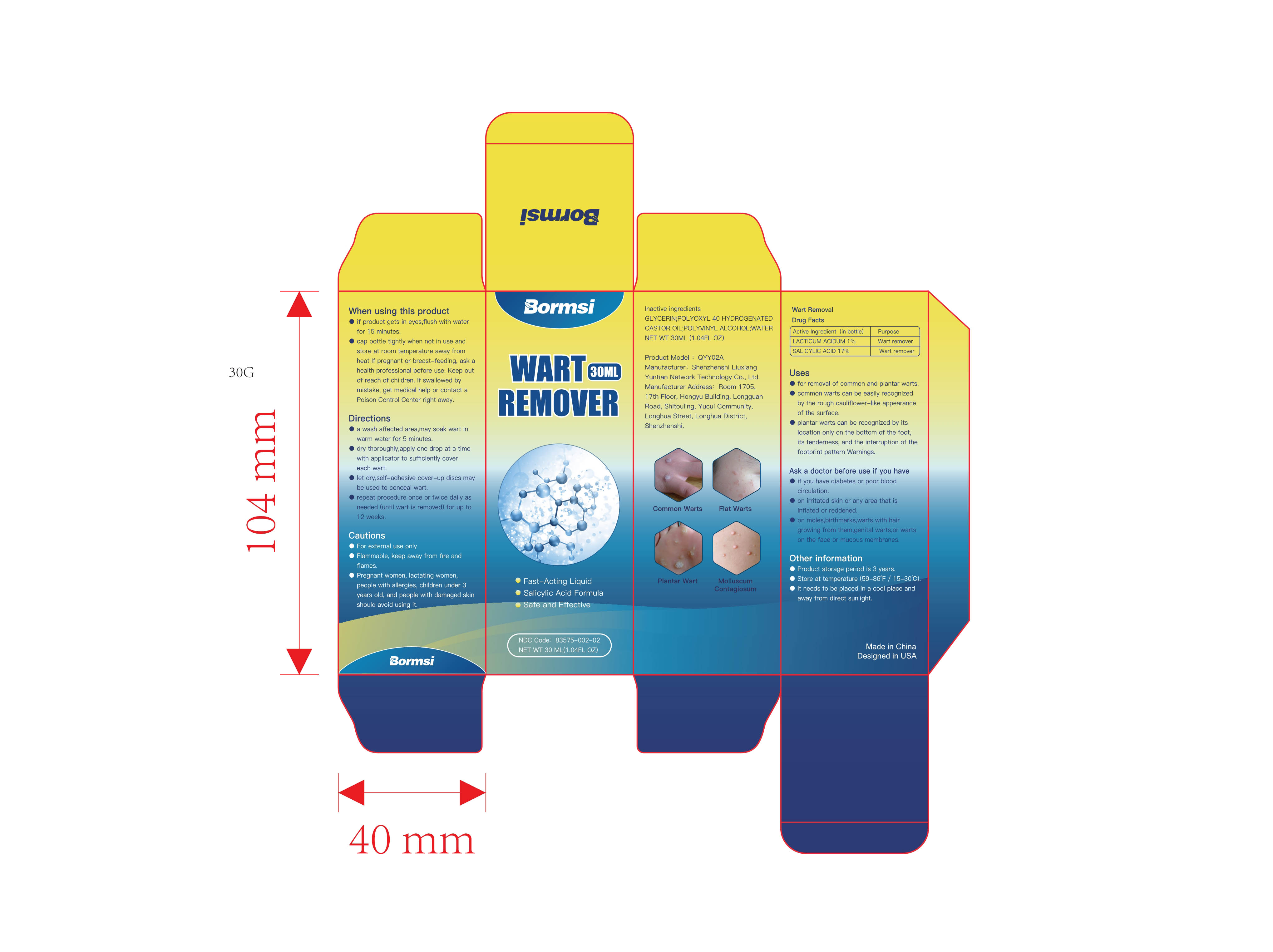 DRUG LABEL: Wart Removal
NDC: 83575-002 | Form: LIQUID
Manufacturer: Shenzhenshi Liuxiang Yuntian Network Technology Co., Ltd.
Category: otc | Type: HUMAN OTC DRUG LABEL
Date: 20231029

ACTIVE INGREDIENTS: SALICYLIC ACID 1 mg/100 mL; LACTIC ACID, DL- 17 mg/100 mL
INACTIVE INGREDIENTS: WATER; GLYCERIN; POLYVINYL ALCOHOL (108000 MW); POLYOXYL 40 HYDROGENATED CASTOR OIL

83575-002

ACTIVE INGREDIENT

SALICYLIC ACID 17%

LACTICUM ACIDUM 1%

Purpose

Wart remover

Uses

- For removal of common and plantar warts.
- Common warts can be easily recognized by the rough cauliflflower-like appearance of the surface
- Plantar warts can be recognized by its location only on the bottom of the foot, its tenderness, and the interruption of the footprint pattern

Warnings

Ask a doctor before use if you have

- If you have diabetes or poor blood circulation
- On irritated skin or any area that is inflflated or reddened
- On moles,birthmarks,warts with hair growing from them, genital warts, or warts on the face or mucous membranes

DO NOT USE

Cautions
- For external use only
- Flammable, keep away from fire and flames
- Pregnant women, lactating women, people with allergies, children under 3 years old, and people with damaged skin should avoid using it

When using this product

- If product gets in eyes,flush with water for 15 minutes
- Cap bottle tightly when not in use and store at room temperature away from heat

If pregnant or breast-feeding, ask a health professional before use.
Keep out of reach of children. If swallowed by mistake, get medical help or contact a Poison Control Center right away.

STOP USE

If swallowed by mistake, get medical help or contact a Poison Control Center right away.

Keep out of reach of children.

Directions

- a wash affected area , may soak wart in warmwater for 5 minuteso

- dry thoroughly, apply one drop at a time withapplicator to sufficiently cover each wart

- let dry , self-adhesive cover-up discs may beused to conceal wart
- Repeat procedure once or twice daily as needed (until wart is removed) for up to 12 weeks

Other information

- Product storage period is 3 years

- Store at temperature (59-86℉ / 15-30℃).
- It needs to be placed in a cool place and awayfrom direct sunlight

INACTIVE INGREDIENT

GLYCERIN, POLYOXYL 40 HYDROGENATED CASTOR OIL, POLYVINYL ALCOHOL (108000 MW), WATER